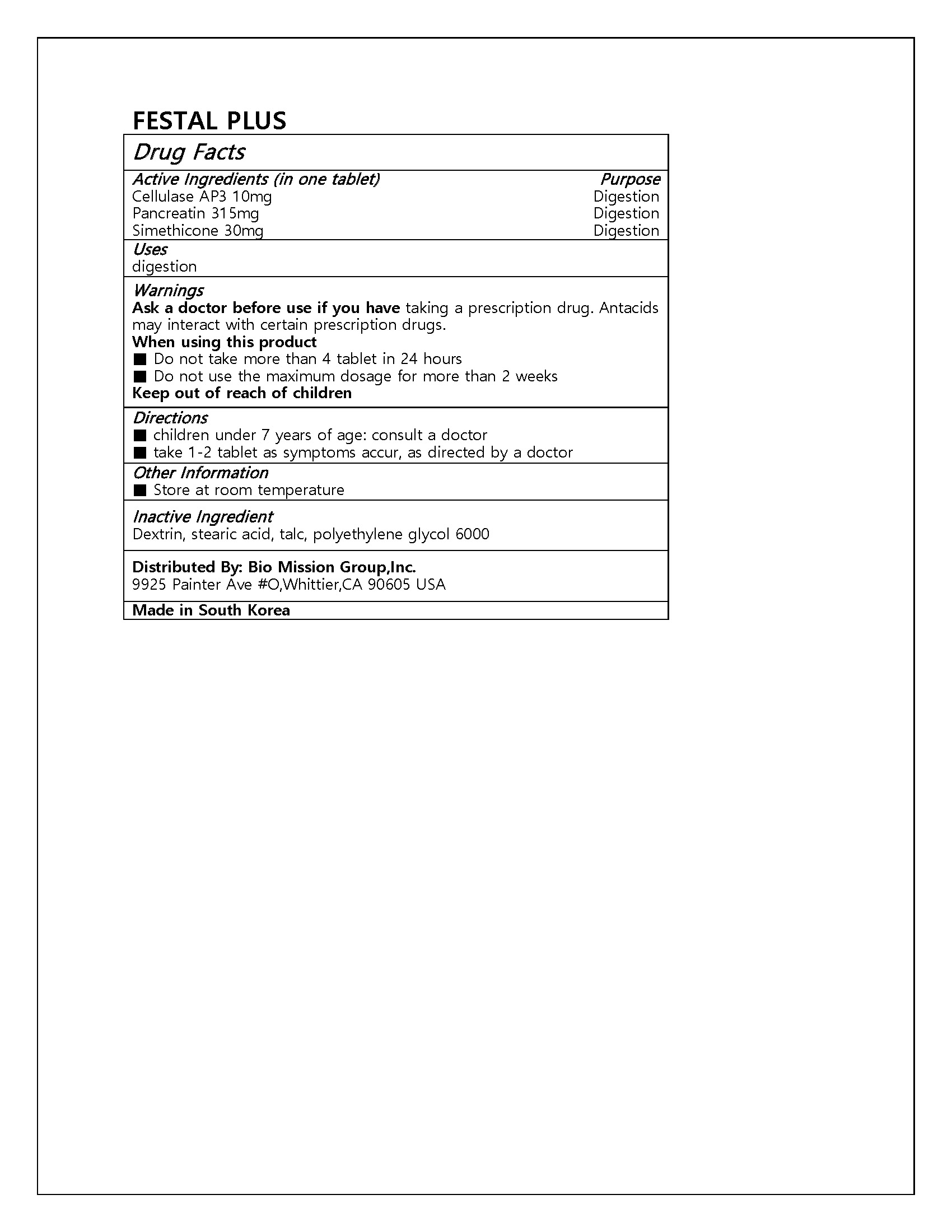 DRUG LABEL: FESTAL PLUS
NDC: 72988-0038 | Form: TABLET
Manufacturer: Lydia Co., Ltd.
Category: otc | Type: HUMAN OTC DRUG LABEL
Date: 20240903

ACTIVE INGREDIENTS: PANCRELIPASE 315 mg/1 1; DIMETHICONE 30 mg/1 1
INACTIVE INGREDIENTS: STEARIC ACID

ACTIVE INGREDIENT

Cellulase AP3

Pancreatin

Simethicone

PURPOSE

digestion

Keep out of reach of children

INDICATIONS AND USAGE

■ children under 7 years of age: consult a doctor

■ take 1-2 tablet as symptoms accur, as directed by a doctor

Ask a doctor before use if you have taking a prescription drug. Antacids may interact with certain prescription drugs.

When using this product

■ Do not take more than 4 tablet in 24 hours

■ Do not use the maximum dosage for more than 2 weeks

Keep out of reach of children

INACTIVE INGREDIENT

Dextrin, stearic acid, talc, polyethylene glycol 6000

DOSAGE AND ADMINISTRATION

for oral use